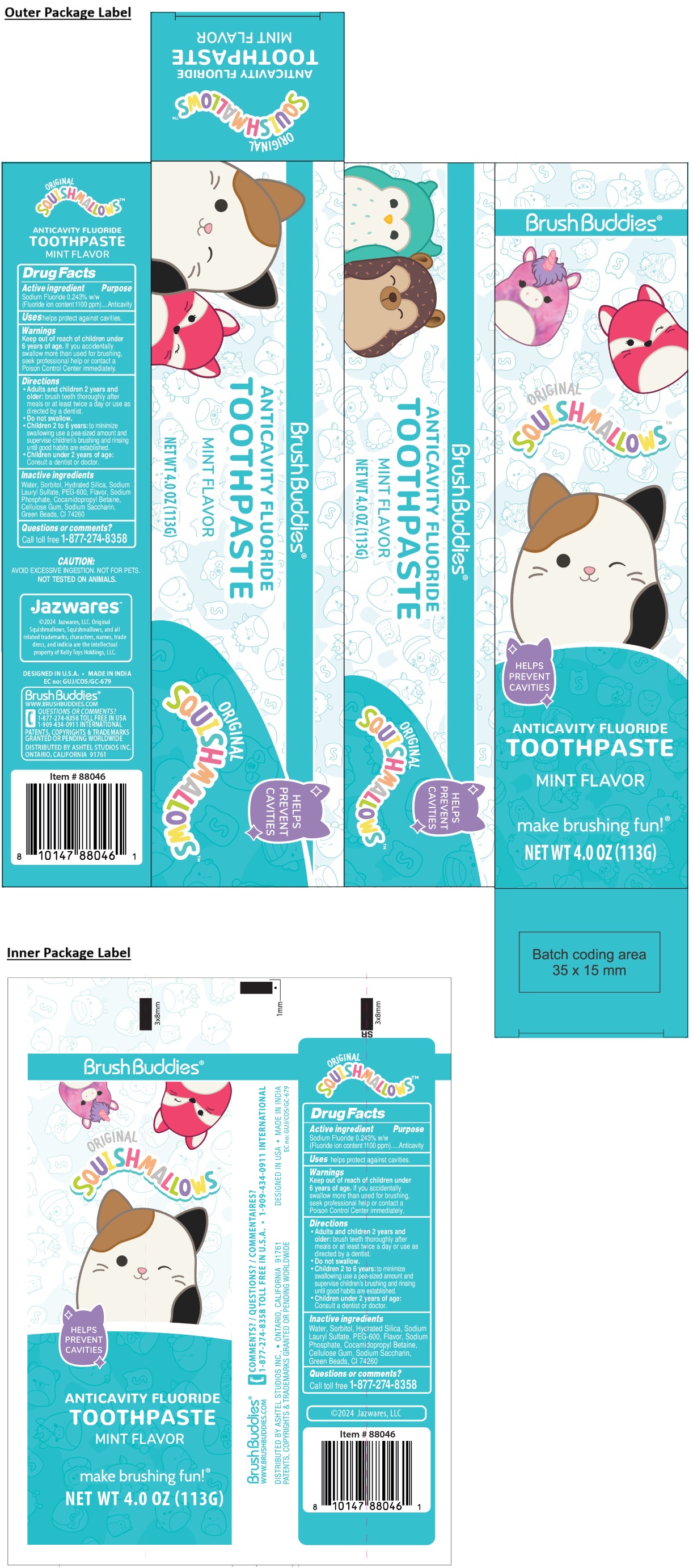 DRUG LABEL: Brush Buddies SQUISHMALLOWS ANTICAVITY FLUORIDE MINT FLAVOR
NDC: 70108-102 | Form: PASTE, DENTIFRICE
Manufacturer: Ashtel Studios Inc.
Category: otc | Type: HUMAN OTC DRUG LABEL
Date: 20240926

ACTIVE INGREDIENTS: SODIUM FLUORIDE 0.243 g/100 g
INACTIVE INGREDIENTS: WATER; SORBITOL; HYDRATED SILICA; SODIUM LAURYL SULFATE; POLYETHYLENE GLYCOL 600; SODIUM PHOSPHATE; COCAMIDOPROPYL BETAINE; CARBOXYMETHYLCELLULOSE SODIUM, UNSPECIFIED; SACCHARIN SODIUM; PIGMENT GREEN 7

Brush Buddies® SQUISHMALLOWS ANTICAVITY FLUORIDE TOOTHPASTE MINT FLAVOR

Active ingredient

Sodium Fluoride 0.243% w/w
(Fluoride ion content 1100 ppm)

Purpose

Anticavity

Uses

helps protect against cavities.

Warnings

Keep out of reach of children under 6 years of age. If you accidentally swallow more than used for brushing, seek professional help or contact a Poison Control Center immediately.

Directions

• Adults and children 2 years and older: brush teeth thoroughly after meals or at least twice a day or use as directed by a dentist.
• Do not swallow.
• Children 2 to 6 years: to minimize swallowing use a pea-sized amount and supervise children's brushing and rinsing until good habits are established.
• Children under 2 years of age: Consult a dentist or doctor.

Inactive ingredients

Water, Sorbitol, Hydrated Silica, Sodium Lauryl Sulfate, PEG-600, Flavor, Sodium Phosphate, Cocamidopropyl Betaine, Cellulose Gum, Sodium Saccharin, Green Beads, CI 74260

Questions or comments?

Call toll free 1-877-274-8358

ORIGINAL

HELPS PREVENT CAVITIES

make brushing fun!®

CAUTION:
AVOID EXCESSIVE INGESTION. NOT FOR PETS.
NOT TESTED ON ANIMALS.

Jazwares™

©2024 Jazwares, LLC. Original Squishmallows, Squishmallows, and all related trademarks, characters, names, trade dress, and indicia are the intellectual property of Kelly Toys Holdings, LLC.

DESIGNED IN U.S.A • MADE IN INDIA

Brush Buddies®
WWW.BRUSHBUDDIES.COM

1-909-434-0911 INTERNATIONAL

PATENTS, COPYRIGHTS & TRADEMARKS GRANTED OR PENDING WORLDWIDE

DISTRIBUTED BY ASHTEL STUDIOS INC.
ONTARIO, CALIFORNIA 91761